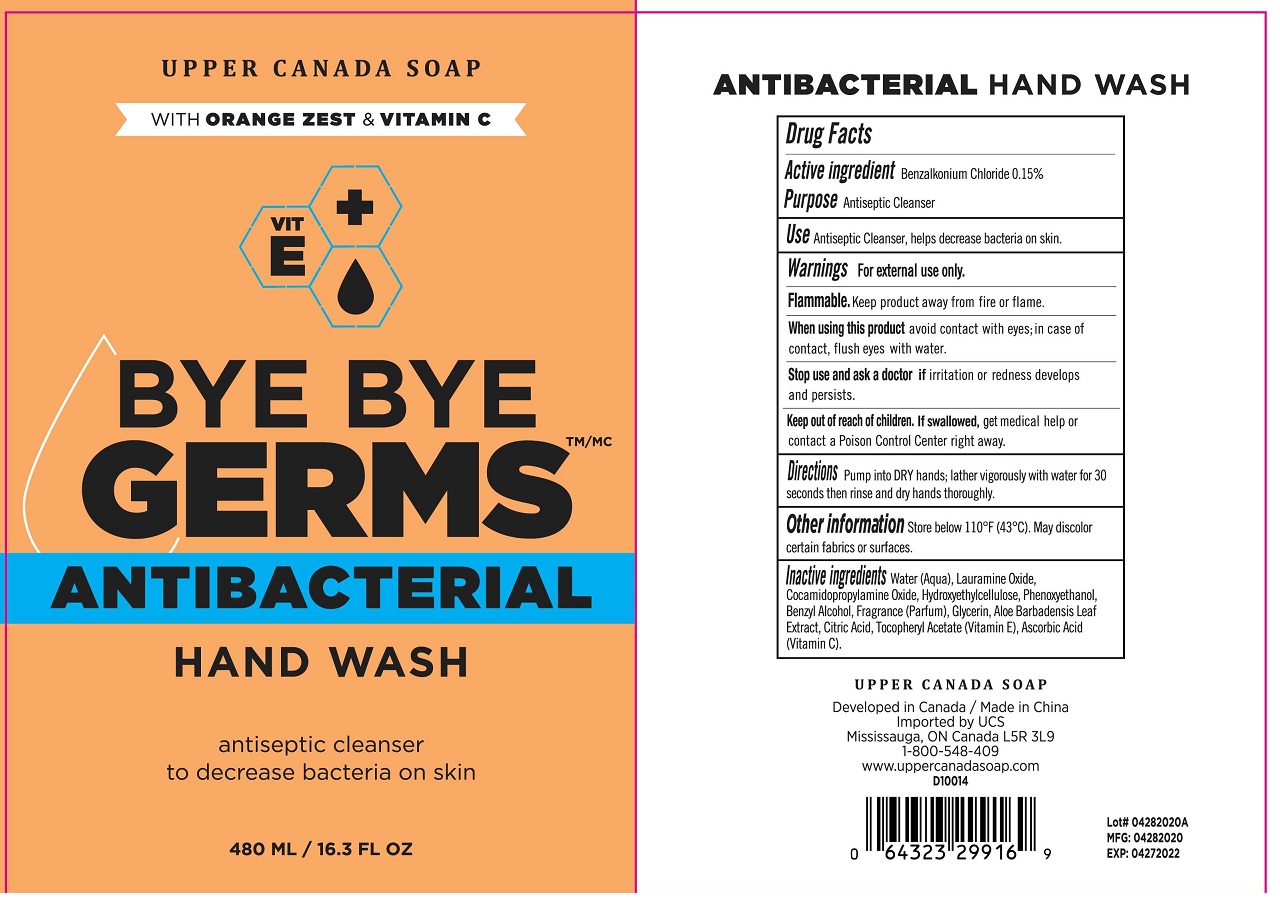 DRUG LABEL: BYE BYE GERMS Antibacterial Hand Wash with Orange Zest and Vitamin C
NDC: 56136-309 | Form: GEL
Manufacturer: Ganzhou Olivee Cosmetic Co., Ltd.
Category: otc | Type: HUMAN OTC DRUG LABEL
Date: 20200430

ACTIVE INGREDIENTS: BENZALKONIUM CHLORIDE 1.5 mg/1 mL
INACTIVE INGREDIENTS: WATER; BUTYLENE GLYCOL; GLYCERIN; CAESALPINIA SPINOSA RESIN; CITRIC ACID MONOHYDRATE; SODIUM LAURYL SULFATE; ETHYLHEXYLGLYCERIN; PHENOXYETHANOL

Hand Wash

Active ingredient

Benzalkonium Chloride 0.15%

Purpose

Antiseptic Cleanser

Use

Antiseptic Cleanser, helps decrease bacteria on skin.

Warnings

For external use only.

Flammable, keep product away from fire or flame.

When using this product

avoi contact with eyes; in case of contact, flush eyes with water.

Stop use and ask a doctor if

- irritation and redness develops and persists.

Keep out of reach of children.

If swallowed, get medical help or contact a Poison Control Center right away.

Directions

Pump into DRY hands; lather vigorously with water for 30 seconds then rinse and dry hands thorougly

Other information

- store below 110℉（43℃). May discolor certain fabrics or surfaces.

Inactive ingredients

Water (Aqua), Lauramine Oxide, Cocamidopropylamine Oxide, Hydroxyethylcellulose, Phenoxyethanol, Benzyl Alcohol, Fragrance (Parfum), glycerin, Aloe Barbadensis Leaf Extract, Citric Acid, Tocopheryl Acetate (Vitamin E), Melaleuca Alternifolia (Tea Tree) Extract.